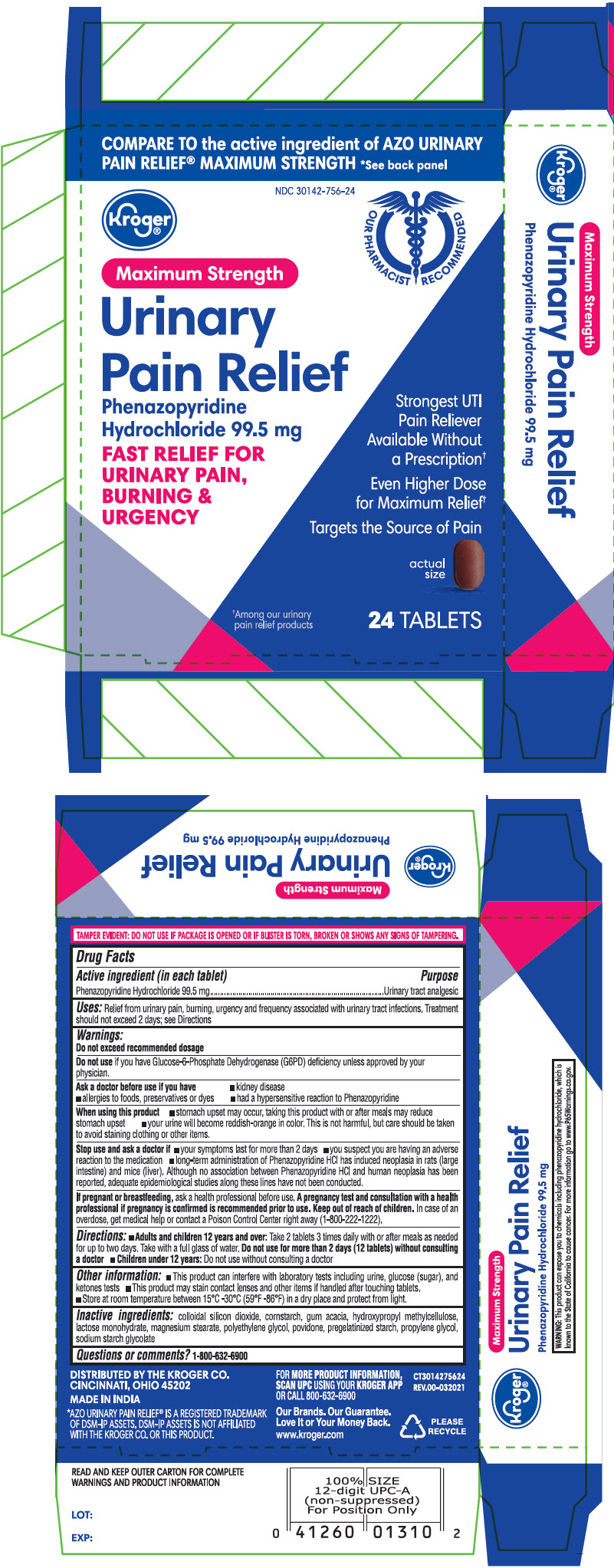 DRUG LABEL: Maximum Strength Urinary Pain Relief
NDC: 30142-756 | Form: TABLET
Manufacturer: KROGER COMPANY
Category: otc | Type: HUMAN OTC DRUG LABEL
Date: 20231230

ACTIVE INGREDIENTS: Phenazopyridine Hydrochloride 99.5 mg/1 1
INACTIVE INGREDIENTS: Silicon Dioxide; Hypromellose, Unspecified; Lactose Monohydrate; Magnesium Stearate; Starch, Corn; Polyethylene Glycol, Unspecified; Povidone, Unspecified; Propylene Glycol; Sodium Starch Glycolate Type A

Maximum Strength Urinary Pain Relief

Drug Facts

Active ingredient (in each tablet)

Phenazopyridine Hydrochloride 99.5 mg

Purpose

Urinary tract analgesic

Uses

Relief from urinary pain, burning, urgency and frequency associated with urinary tract infections. Treatment should not exceed 2 days; see Directions

Warnings

Do not exceed recommended dosage

Do not use if you have Glucose-6-Phosphate Dehydrogenase (G6PD) deficiency unless approved by your physician.

Ask a doctor before use if you have

- kidney disease
- allergies to foods, preservatives or dyes
- had a hypersensitive reaction to Phenazopyridine

When using this product

- stomach upset may occur, taking this product with or after meals may reduce stomach upset
- your urine will become reddish-orange in color. This is not harmful, but care should be taken to avoid staining clothing or other items.

Stop use and ask a doctor if

- your symptoms last for more than 2 days
- you suspect you are having an adverse reaction to the medication
- long-term administration of Phenazopyridine HCl has induced neoplasia in rats (large intestine) and mice (liver). Although no association between Phenazopyridine HCl and human neoplasia has been reported, adequate epidemiological studies along these lines have not been conducted.

PREGNANCY OR BREAST FEEDING

If pregnant or breastfeeding, ask a health professional before use.A pregnancy test and consultation with a health professional if pregnancy is confirmed is recommended prior to use.

Keep out of reach of children. In case of an overdose, get medical help or contact a Poison Control Center right away.

Directions

- Adults and children 12 years and over: Take 2 tablets 3 times daily with or after meals as needed for up to two days. Take with a full glass of water. Do not use for more than 2 days (12 tablets) without consulting a doctor
- Children under 12 years: Do not use without consulting a doctor

Other information

- This product can interfere with laboratory tests including urine, glucose (sugar), and ketones tests
- This product may stain contact lenses and other items if handled after touching tablets.
- Store at room temperature between 15°C -30°C (59°F -86°F) in a dry place and protect from light.

Inactive ingredients

colloidal silicone dioxide, gum acacia extra pure, hydroxy propyl methyl cellulose, lactose monohydrate, magnesium stearate, maize starch, polyethylene glycol, povidone, pregelatinized starch, propylene glycol, sodium starch glycolate

Questions or comments?

call 1-800-632-6900

DISTRIBUTED BY THE KROGER CO.
CINCINNATI, OHIO 45202

PRINCIPAL DISPLAY PANEL - 99.5 mg Tablet Blister Pack Carton

COMPARE TO the active ingredient of AZO® URINARY
PAIN RELIEF® MAXIMUM STRENGTH *See back panel

NDC 30142-756-24

Kroger®

OUR PHARMACIST RECOMMENDED

Maximum Strength

Urinary
Pain Relief

Phenazopyridine
Hydrochloride 99.5 mg

FAST RELIEF FOR
URINARY PAIN,
BURNING &
URGENCY

Strongest UTI
Pain Reliever
Available Without
a Prescription†

Even Higher Dose
for Maximum Relief†

Targets the Source of Pain

actual
size

†Among our urinary
pain relief products

24 TABLETS